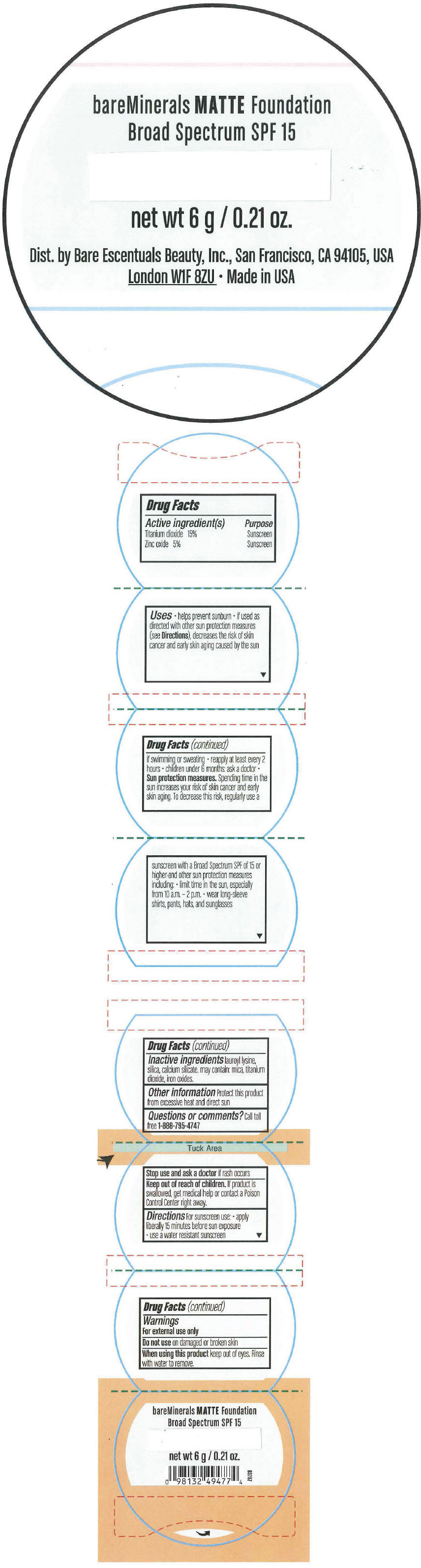 DRUG LABEL: bareMinerals Matte Foundation Broad Spectrum SPF 15 
NDC: 98132-151 | Form: POWDER
Manufacturer: Bare Escentuals Beauty Inc.
Category: otc | Type: HUMAN OTC DRUG LABEL
Date: 20170315

ACTIVE INGREDIENTS: Titanium Dioxide 15 g/100 g; Zinc Oxide 5 g/100 g
INACTIVE INGREDIENTS: LAUROYL LYSINE; Calcium Silicate; Mica; Ferric Oxide Red; Silicon Dioxide

bareMinerals Matte Foundation Broad Spectrum SPF 15

Drug Facts

ACTIVE INGREDIENT

Active ingredient(s) | Purpose
Titanium dioxide 15% | Sunscreen
Zinc oxide 5% | Sunscreen

Uses

- helps prevent sunburn
- if used as directed with other sun protection measures (see Directions), decreases the risk of skin cancer and early skin aging caused by the sun

Warnings

For external use only

Do not use on damaged or broken skin

When using this product keep out of eyes. Rinse with water to remove.

Stop use and ask a doctor if rash occurs

Keep out of reach of children. If product is swallowed, get medical help or contact a Poison Control Center right away.

Directions

For sunscreen use:

- apply liberally 15 minutes before sun exposure
- use a water resistant sunscreen if swimming or sweating
- reapply at least every 2 hours
- children under 6 months: ask a doctor
- Sun protection measures. Spending time in the sun increases your risk of skin cancer and early skin aging. To decrease this risk, regularly use a sunscreen with a Broad Spectrum SPF of 15 or higher-and other sun protection measures including:
  - limit time in the sun, especially from 10 a.m. - 2 p.m.
  - wear long-sleeve shirts, pants, hats, and sunglasses

Inactive ingredients

lauroyl lysine, silica, calcium silicate. may contain: mica, titanium dioxide, iron oxides.

Other information

Protect this product from excessive heat and direct sun

Questions or comments?

Call toll free 1-888-795-4747

Dist. by Bare Escentuals Beauty, Inc., San Francisco, CA 94105, USA

PRINCIPAL DISPLAY PANEL - 6 g Jar Label - Golden Fair

bareMinerals MATTE Foundation
Broad Spectrum SPF 15

net wt 6 g / 0.21 oz.

Dist. by Bare Escentuals Beauty, Inc., San Francisco, CA 94105, USA
London W1F 8ZU • Made in USA

PRINCIPAL DISPLAY PANEL - 6 g Jar Label - Fairly Medium

bareMinerals MATTE Foundation
Broad Spectrum SPF 15

net wt 6 g / 0.21 oz.

Dist. by Bare Escentuals Beauty, Inc., San Francisco, CA 94105, USA
London W1F 8ZU • Made in USA

PRINCIPAL DISPLAY PANEL - 6 g Jar Label - Warm Dark

bareMinerals MATTE Foundation
Broad Spectrum SPF 15

net wt 6 g / 0.21 oz.

Dist. by Bare Escentuals Beauty, Inc., San Francisco, CA 94105, USA
London W1F 8ZU • Made in USA